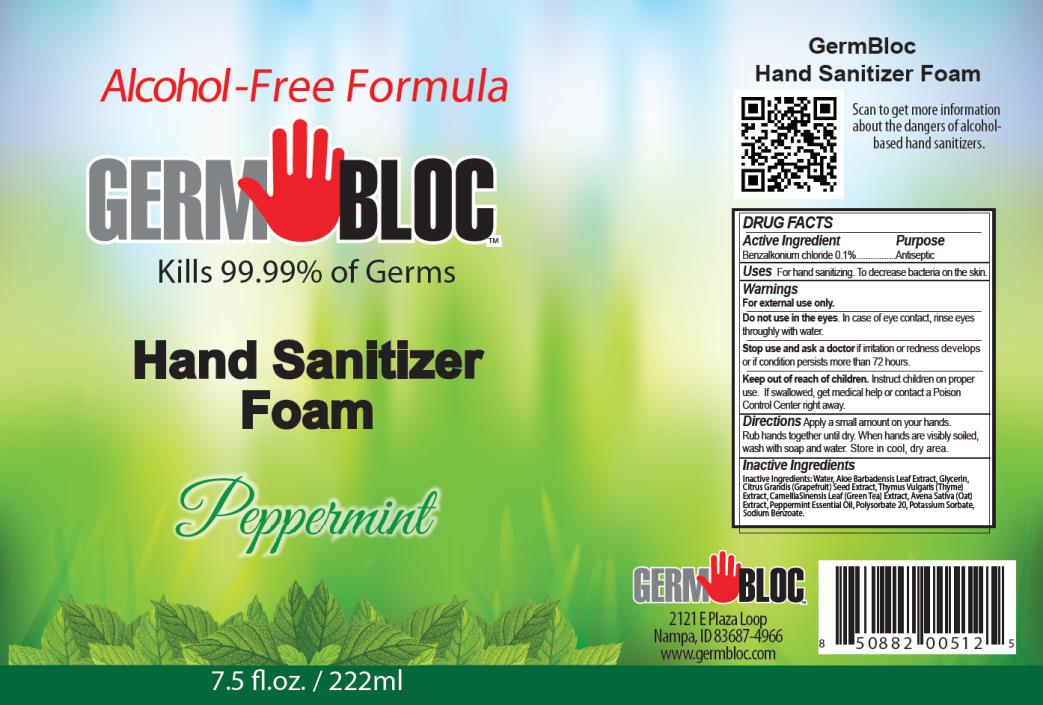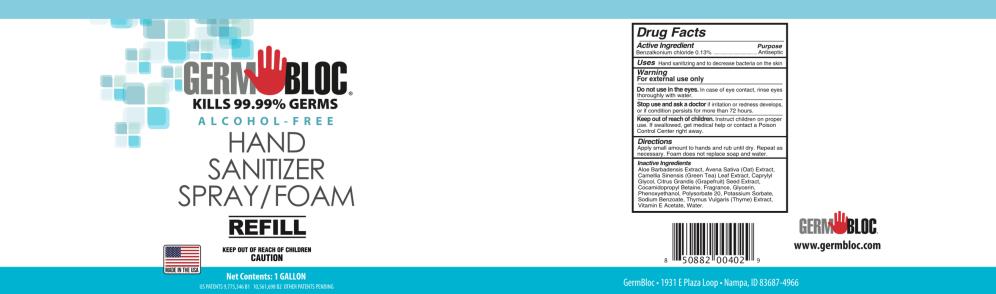 DRUG LABEL: Germ Bloc Hand Sanitizer Foam Peppermint
NDC: 69243-0710 | Form: LIQUID
Manufacturer: Willspeed Technologies LLC
Category: otc | Type: HUMAN OTC DRUG LABEL
Date: 20220114

ACTIVE INGREDIENTS: BENZALKONIUM CHLORIDE 0.001 g/1 mL
INACTIVE INGREDIENTS: WATER; ALOE VERA LEAF; GLYCERIN; CITRUS MAXIMA SEED; THYME; GREEN TEA LEAF; AVENA SATIVA LEAF; PEPPERMINT OIL; POLYSORBATE 20; POTASSIUM SORBATE; SODIUM BENZOATE

Germ Bloc Hand Sanitizer Foam

DRUG FACTS

Active Ingredient

Benzalkonium chloride 0.1%

Purpose

Antiseptic

Uses

For hand sanitizing. To decrease bacteria on the skin.

Warnings

For external use only.

Do not use in the eyes.

In case of eye contact, rinse eyes thoroughly with water.

Stop use and ask a doctor

if irritation or redness develops or if condition persists more than 72 hours.

Keep out of reach of children.

Instruct children on proper use. If swallowed, get medical help or contact a Poison Control Center right away.

Directions

Apply a small amount on your hands. Rub hands together until dry. When hands are visibly soiled, wash with soap and water. Store in cool, dry area.

Inactive Ingredients

Water, Aloe Barbadensis Leaf Extract, Glycerin, Citrus Grandis (Grapefruit) Seed Extract, Thymus Vulgaris (Thyme) Extract, Camellia Sinensis Leaf (Green Tea) Extract, Avena Sativa (Oat) Extract, Peppermint Essential Oil, Polysorbate 20, Potassium Sorbate, Sodium Benzoate.

DRUG FACTS

Active Ingredient

Benzalkonium chloride 0.1%

Purpose

Antiseptic

Uses

For hand sanitizing. To decrease bacteria on the skin.

Warnings

For external use only.

Do not use in the eyes.

In case of eye contact, rinse eyes thoroughly with water.

Stop use and ask a doctor

if irritation or redness develops or if condition persists more than 72 hours.

Keep out of reach of children.

Instruct children on proper use. If swallowed, get medical help or contact a Poison Control Center right away.

Directions

Apply a small amount on your hands. Rub hands together until dry. When hands are visibly soiled, wash with soap and water. Store in cool, dry area.

Inactive Ingredients

Aloe Barbadensis Extract, Avena Sativa (Oat) Extract, Camellia Sinensis (Green Tea) Leaf Extract, Caprylyl Glycol, Citrus Grandis (Grapefruit) Seed Extract, Cocamidopropyl Betaine, Fragrance, Glycerin, Phenoxyethanol, Polysorbate 20, Potassium Sorbate, Sodium Benzoate, Thymus Vulgaris (Thyme) Extract, Vitamin E Acetate, Water

PRINCIPAL DISPLAY PANEL

Alcohol-Free Formula
GERM BLOCTM
Kills 99.99% of Germs
Hand Sanitizer
Foam
Peppermint
7.5 fl. oz. / 222 ml

PRINCIPAL DISPLAY PANEL

GERM BLOC®
KILLS 99.99% GERMS
ALCOHOL-FREE
HAND SANITIZER
SPRAY/FOAM
REFILL
Net Contents: 1 GALLON